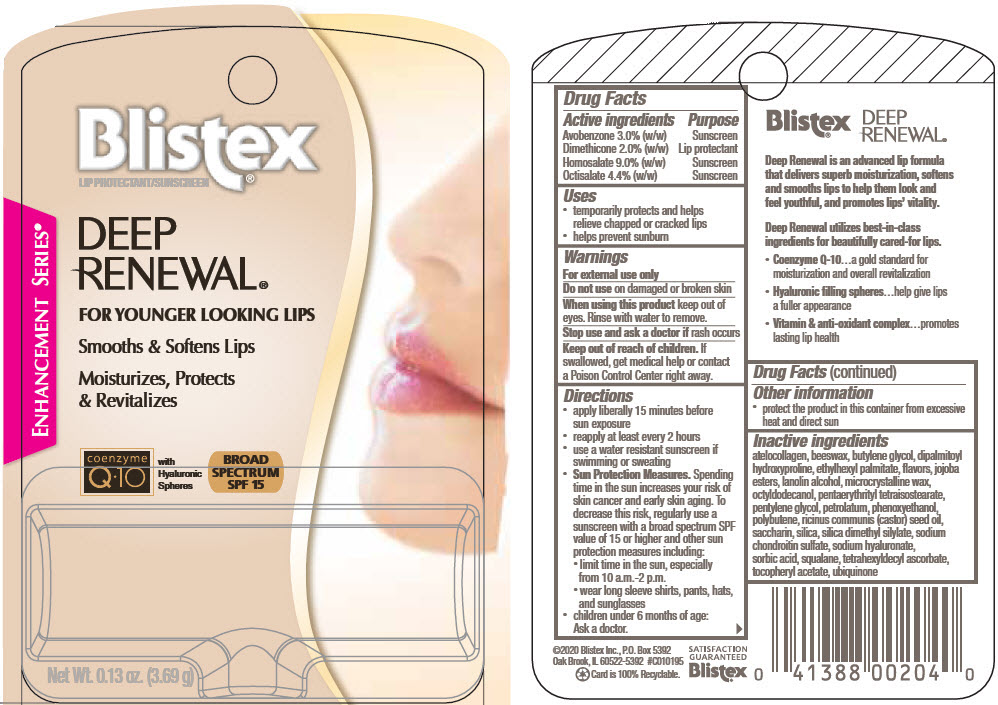 DRUG LABEL: Deep Renewal Broad Spectrum
NDC: 10157-1170 | Form: STICK
Manufacturer: Blistex Inc
Category: otc | Type: HUMAN OTC DRUG LABEL
Date: 20241210

ACTIVE INGREDIENTS: DIMETHICONE 2 g/100 g; AVOBENZONE 3 g/100 g; HOMOSALATE 9 g/100 g; OCTISALATE 4.4 g/100 g
INACTIVE INGREDIENTS: OCTYLDODECANOL; PETROLATUM; HYDROGENATED JOJOBA OIL, RANDOMIZED; MICROCRYSTALLINE WAX; CASTOR OIL; YELLOW WAX; POLYBUTENE (1400 MW); ETHYLHEXYL PALMITATE; SILICA DIMETHYL SILYLATE; BUTYLENE GLYCOL; HYALURONATE SODIUM; DIPALMITOYL HYDROXYPROLINE; SQUALANE; .ALPHA.-TOCOPHEROL ACETATE; LANOLIN ALCOHOLS; PENTAERYTHRITYL TETRAISOSTEARATE; CHONDROITIN SULFATE SODIUM, SHARK; MARINE COLLAGEN, SOLUBLE; PENTYLENE GLYCOL; SILICON DIOXIDE; TETRAHEXYLDECYL ASCORBATE; SACCHARIN; PHENOXYETHANOL; SORBIC ACID; UBIDECARENONE

Deep Renewal® Broad Spectrum

Drug Facts

ACTIVE INGREDIENT

Active ingredients | Purpose
Avobenzone 3.0% (w/w) | Sunscreen
Dimethicone 2.0% (w/w) | Lip protectant
Homosalate 9.0% (w/w) | Sunscreen
Octisalate 4.4% (w/w) | Sunscreen

Uses

- temporarily protects and helps relieve chapped or cracked lips
- helps prevent sunburn

Warnings

For external use only

Do not use on damaged or broken skin

When using this product keep out of eyes. Rinse with water to remove.

Stop use and ask a doctor if rash occurs

Keep out of reach of children. If swallowed, get medical help or contact a Poison Control Center right away.

Directions

- apply liberally 15 minutes before sun exposure
- reapply at least every 2 hours
- use a water resistant sunscreen if swimming or sweating
- Sun Protection Measures. Spending time in the sun increases your risk of skin cancer and early skin aging. To decrease this risk, regularly use a sunscreen with a broad spectrum SPF value of 15 or higher and other sun protection measures including:
  - limit time in the sun, especially from 10 a.m.-2 p.m.
  - wear long sleeve shirts, pants, hats, and sunglasses
- children under 6 months of age: Ask a doctor.

Other information

- protect the product in this container from excessive heat and direct sun

Inactive ingredients

atelocollagen, beeswax, butylene glycol, dipalmitoyl hydroxyproline, ethylhexyl palmitate, flavors, jojoba esters, lanolin alcohol, microcrystalline wax, octyldodecanol, pentaerythrityl tetraisostearate, pentylene glycol, petrolatum, phenoxyethanol, polybutene, ricinus communis (castor) seed oil, saccharin, silica, silica dimethyl silylate, sodium chondroitin sulfate, sodium hyaluronate, sorbic acid, squalane, tetrahexyldecyl ascorbate, tocopheryl acetate, ubiquinone

PRINCIPAL DISPLAY PANEL - 3.69 g Cylinder Blister Pack

Blistex®
LIP PROTECTANT/SUNSCREEN

DEEP
RENEWAL®

FOR YOUNGER LOOKING LIPS

Smooths & Softens Lips

Moisturizes, Protects
& Revitalizes

ENHANCEMENT SERIES®

coenzyme
Q∙10

with
Hyaluronic
Spheres

BROAD
SPECTRUM
SPF 15

Net Wt. 0.13 oz. (3.69 g)